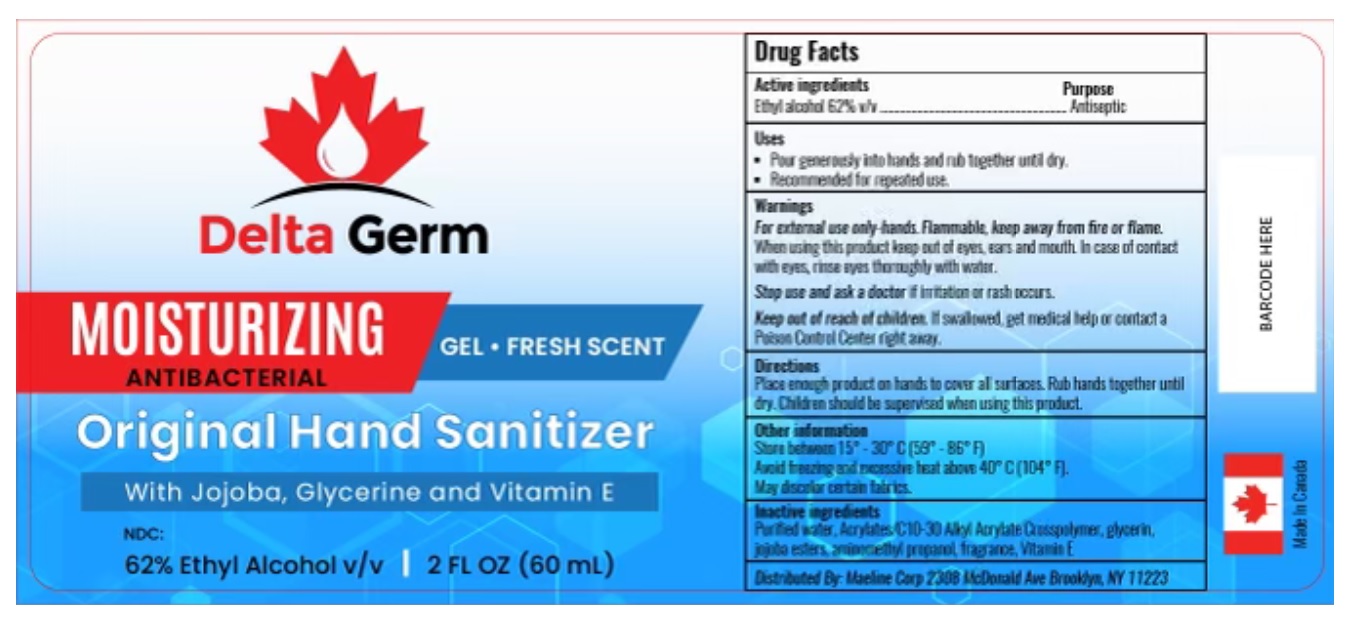 DRUG LABEL: Delta Germ Hand Sanitizer
NDC: 79861-004 | Form: GEL
Manufacturer: Sanihealth Labs Inc.
Category: otc | Type: HUMAN OTC DRUG LABEL
Date: 20210105

ACTIVE INGREDIENTS: ALCOHOL 0.62 mL/1 mL
INACTIVE INGREDIENTS: AMINOMETHYLPROPANOL; WATER; GLYCERIN; .ALPHA.-TOCOPHEROL ACETATE; HYDROLYZED JOJOBA ESTERS (ACID FORM); CARBOMER INTERPOLYMER TYPE A (55000 CPS)

Delta Germ Hand Sanitizer

Active Ingredients

Ethyl Alcohol 62%v/v.

Purpose: Antiseptic

Purpose

Antiseptic

Uses

- helps reduce bacteria on the skin that could cause disease

Directions

- Place enough product in your palm to thoroughly cover your hands
- Rub hands together briskly until dry
- Children should be supervised when using this product.
- For personal and occasional domestic use

Warnings

For external use only.

Flammable. Keep away from fire or flame.

KEEP OUT OF REACH OF CHILDREN

If swallowed, get medical help or contact Poison Control right away

Ask Doctor

Stop Use and Ask a doctor if irritation or redness develops

Safety Instructions

Flammable, Keep away from fire and flame

Other Information

Store below 15-30°C
May discolor certain fabrics or surfaces.

Avoid freezing and excessive heat

Inactive Ingredients

water, hydrolyzed jojoba esters, glycerin, Acrylates C10-30 Alkyl Acrylate Crosspolymer, fragrance, aminomethyl propanol, Vitamin E